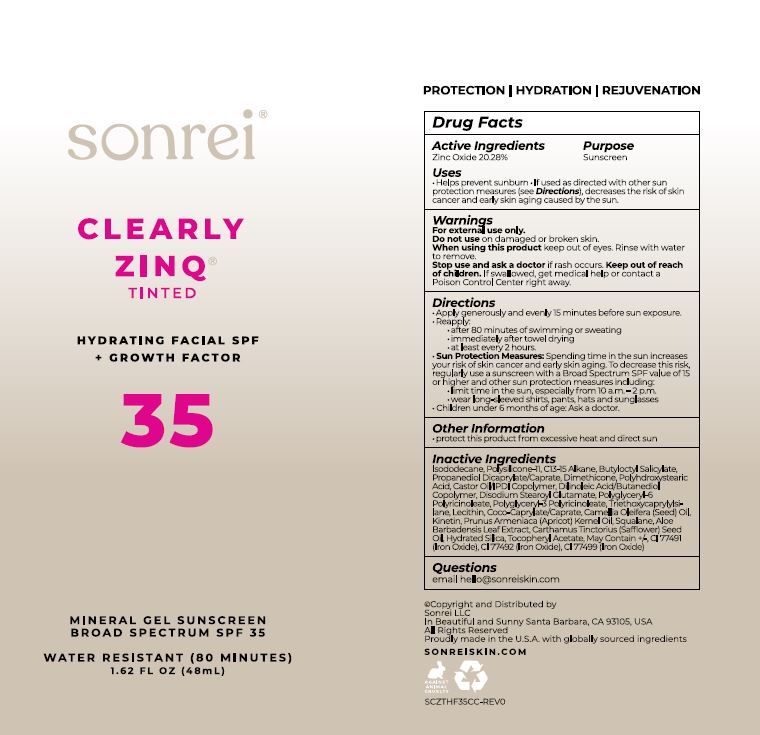 DRUG LABEL: Clearly Zinq Tinted Hydrating Facial SPF Growth Factor 35
NDC: 62742-4259 | Form: CREAM
Manufacturer: Allure Labs
Category: otc | Type: HUMAN OTC DRUG LABEL
Date: 20240404

ACTIVE INGREDIENTS: ZINC OXIDE 20.28 g/100 g
INACTIVE INGREDIENTS: DIMETHICONE; CASTOR OIL; DIMETHICONE/VINYL DIMETHICONE CROSSPOLYMER (SOFT PARTICLE); C13-15 ALKANE; POLYGLYCERYL-6 POLYRICINOLEATE; SAFFLOWER OIL; HYDRATED SILICA; COCO-CAPRYLATE/CAPRATE; .ALPHA.-TOCOPHEROL ACETATE; FERROSOFERRIC OXIDE; ISODODECANE; KINETIN; CAMELLIA OIL; APRICOT KERNEL OIL; SQUALANE; FERRIC OXIDE YELLOW; FERRIC OXIDE RED; BUTYLOCTYL SALICYLATE; ALOE VERA LEAF; LECITHIN, SOYBEAN; PROPANEDIOL DICAPRYLATE/CAPRATE; DISODIUM STEAROYL GLUTAMATE; POLYGLYCERYL-3 PENTARICINOLEATE; DILINOLEIC ACID/BUTANEDIOL COPOLYMER; TRIETHOXYCAPRYLYLSILANE; POLYHYDROXYSTEARIC ACID (2300 MW)

Drug Facts

Active ingredients:

Zinc Oxide 20.28%

Purpose: Sunscreen

INDICATIONS AND USAGE

Uses • Helps prevent sunburn • If used as directed with other sun protection measures (see Directions), decreases the risk of skin cancer and early skin aging caused by the sun.

Warnings: For external use only.

Do not use on damaged or broken skin.

When using this product keep out of eyes. Rinse with water to remove.

Stop use and ask a doctor if rash occurs.

Keep out of reach of children. If swallowed, get medical help or contact a Poison Control Center right away.

DOSAGE AND ADMINISTRATION

Directions •Apply generously and evenly15 minutes before sun exposure. • Reapply: • after 80 minutes of swimming or sweating • immediately after towel drying • at least every 2 hours. • Sun Protection Measures Spending time in the sun increases your risk of skin cancer and early skin aging. To decrease this risk, regularly use a sunscreen with a Broad Spectrum SPF value of 15 or higher time in the sun, especially from 10 a.m. -2 p.m., •wear long-sleeved shirts, pants, hats and sunglasses • Children under 6 months of age: Ask a doctor.

Other information • protect this product from excessive heat and direct sun.

Inactive ingredients:

Isododecane, Polysilicone-11, C13-15 Alkane, Butyloctyl Salicylate, Propanediol Dicaprylate/Caprate, Dimethicone, Polyhydroxystearic Acid, Castor oil/IPDI Copolymer, Dilinoleic Acid/Butanediol Copolymer, Disodium Stearoyl Glutamate, Polyglyceryl-6 Polyricinoleate, Polyglyceryl-3 Polyricinoleate, Triethoxycaprylylsilane, Lecithin, Coco-Caprylate/Caprate, Camellia Oleifera (Seed) Oil, Kinetin, Prunus Armeniaca (Apricot) Kernel Oil, Squalane,Aloe Barbadensis Leaf Extract, Carthamus Tinctorius (Safflower) Seed Oil, Hydrated Silica, Tocopheryl Acetate, May Contain +/-, CI 77491 (Iron Oxide), CI 77492 (Iron Oxide), CI 77499 (Iron Oxide)